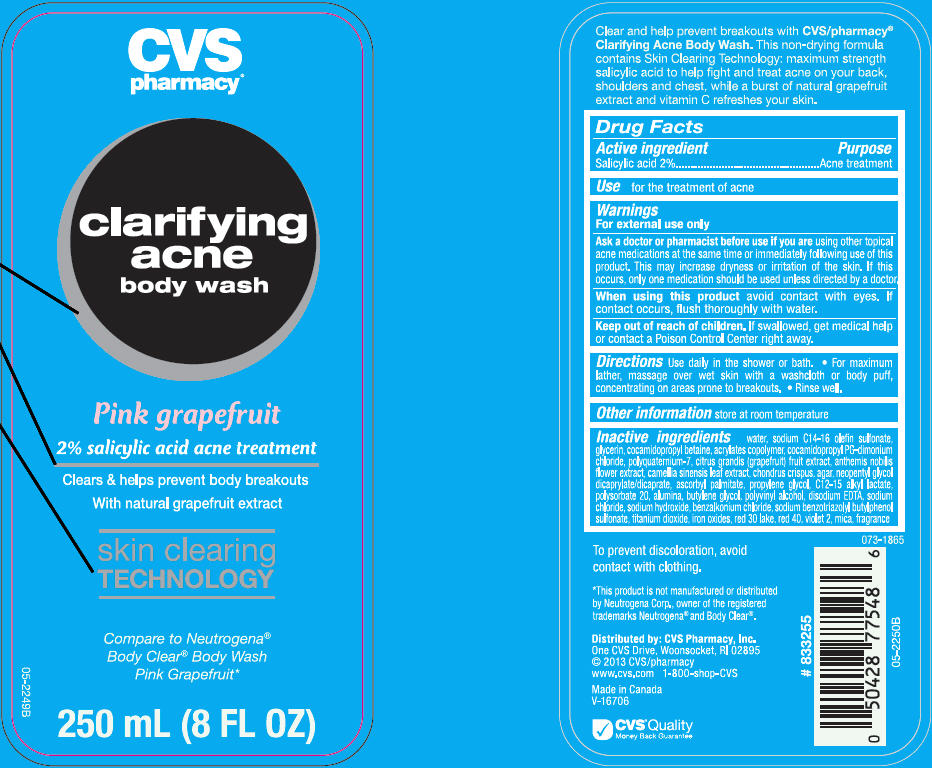 DRUG LABEL: CVS Clarifying Acne Body Wash-Pink Grapefruit
NDC: 69842-457 | Form: LOTION
Manufacturer: CVS Health
Category: otc | Type: HUMAN OTC DRUG LABEL
Date: 20241112

ACTIVE INGREDIENTS: Salicylic Acid 20 mg/1 mL
INACTIVE INGREDIENTS: Water; Sodium C14-16 Olefin Sulfonate; Cocamidopropyl Betaine; Polyquaternium-7 (70/30 Acrylamide/Dadmac; 1600000 MW); Cocamidopropyl Propylene Glycol-Dimonium Chloride Phosphate; Pummelo; Chamaemelum Nobile Flower; Green Tea Leaf; Chondrus Crispus; Agar, Unspecified; Neopentyl Glycol Dicaprylate/Dicaprate; Ascorbyl Palmitate; Propylene Glycol; C12-15 Alkyl Lactate; Polysorbate 20; Aluminum Oxide; Butylene Glycol; Polyvinyl Alcohol (100000 MW); Edetate Disodium; Sodium Chloride; Sodium Hydroxide; Benzalkonium Chloride; Sodium Benzotriazolyl Butylphenol Sulfonate; Titanium Dioxide; Ferric Oxide Red; D&C Red No. 30; Fd&C Red No. 40; D&C Violet No. 2; Mica

CVS Clarifying Acne Body Wash-Pink Grapefruit
Acne Treatment

Active ingredients

Salicylic Acid 2.0%

Purpose

Acne Treatment

Use

For the treatment of acne

Warnings

For external use only

Ask a doctor or pharmacist before use if you are using other topical acne medications at the same time or immediately following use of this product. This may increase dryness or irritation of the skin. If this occurs, only one medication should be used unless directed by a doctor.

When using this product avoid contact with eyes. If contact occurs, flush thoroughly with water.

Keep out of reach of children. If swallowed, get medical help or contact a Poison Control Center right away.

Directions

- Use daily in the shower or bath
- For maximum lather, massage over wet skin with a washcloth or body puff, concentrating on areas prone to breakouts
- Rinse well.

Inactive ingredients

Water, Sodium C14-16 Olefin Sulfonate, Cocamidopropyl Betaine, Acrylates Copolymer, Cocamidopropyl PG-dimonium Chloride, Polyquaternium-7, Citrus Grandis (Grapefruit) Fruit Extract, Anthemis Nobilis Flower Extract, Camellia Sinensis Leaf Extract, Chondrus Crispus, Agar, Neopentyl Glycol Dicaprylate/Dicaprate, Ascorbyl Palmitate, Propylene Glycol, C12-15 Alkyl Lactate, Polysorbate 20, Alumina, Butylene Glycol, Polyvinyl Alcohol, Disodium EDTA, Sodium Chloride, Sodium Hydroxide, Benzalkonium Chloride, Sodium Benzotriazolyl Butylphenol Sulfonate, Titanium Dioxide, Iron Oxides, Red 30 Lake, Red 40, Violet 2, Mica, Fragrance.

Distributed by: CVS Pharmacy, Inc.
One CVS Drive, Woonsocket, RI 02895

PRINCIPAL DISPLAY PANEL - 250 mL Bottle Label

CVS
pharmacy®

clarifying
acne
body wash

Pink grapefruit
2% salicylic acid acne treatment

Clears & helps prevent body breakouts
With natural grapefruit extract

skin clearing
TECHNOLOGY

Compare to Neutrogena®
Body Clear® Body Wash
Pink Grapefruit*

250 mL (8 FL OZ)

05-2249B